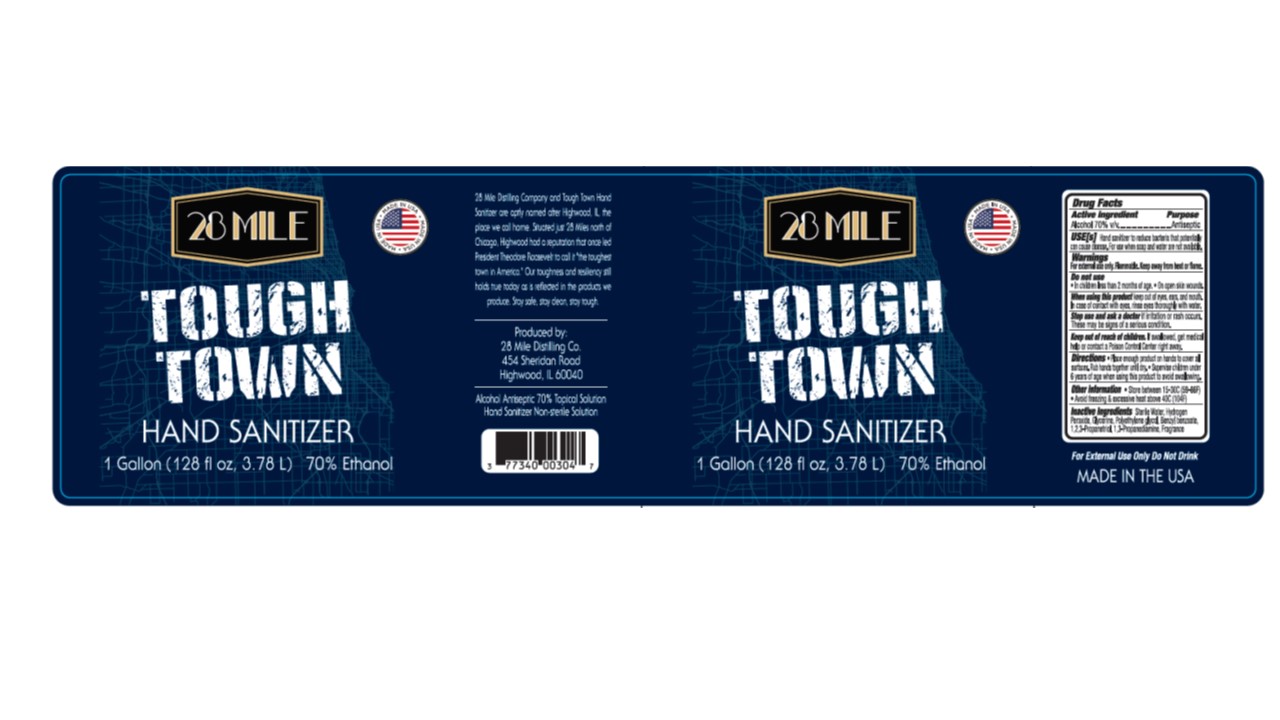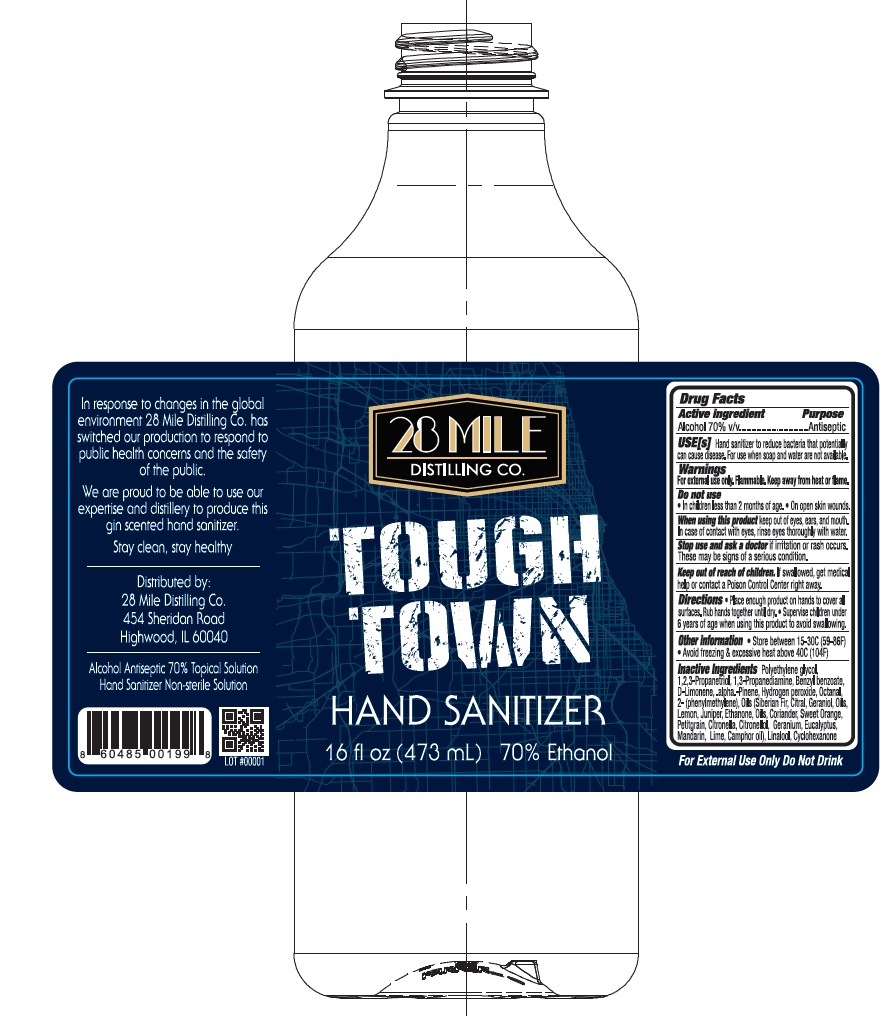 DRUG LABEL: Tough town Hand Sanitizer
NDC: 77340-003 | Form: GEL
Manufacturer: 28 MILE DISTILLING COMPANY, LLC
Category: otc | Type: HUMAN OTC DRUG LABEL
Date: 20201002

ACTIVE INGREDIENTS: ALCOHOL 70 mL/100 mL
INACTIVE INGREDIENTS: WATER; HYDROGEN PEROXIDE; GLYCERIN; 1,2,3-PROPANETRIOL, 2-(4-AMINOBENZOATE)

Active Ingredient

Alcohol 70% v/v.

Purpose

Antiseptic

Uses

Hand Sanitizer to help reduce bacteria that potentially can cause disease. For use when soap and water are not available.

Warnings

For external use only. Flammable. Keep away from heat or flame.

When using this product keep out of eyes, ears, and mouth. In case of contact with eyes, rinse eyes thoroughly with water.
Stop use and ask a doctor if irritation or rash occurs. These may be signs of a serious condition.

Keep out of reach of children. If swallowed, get medical help or contact a Poison Control Center right away.

Directions

- Place enough product on hands to cover all surfaces. Rub hands together until dry.
- Supervise children under 6 years of age when using this product to avoid swallowing.

Other information

- Store between 15-30C (59-86F)
- Avoid freezing and excessive heat above 40C (104F)

For external use only, do not drink.

Inactive ingredients

Polyethylene glycol,1, 2, 3-Propanetriol, 1 ,3-Propanediamine, Benzyl benzoate, D-Limonene, .alpha.-Pinene, Hydrogen peroxide, Octanal, 2- (phenylmethylene), Oils (Siberian Fir, Citral, Geraniol Oils, Lemon, Juniper, Ethanone, Oils, Coriander, Sweet Orange, Petitgrain, Citronella, Citronellol, Geranium, Eucalyptus, Mandarin, Lime, Camphor oil, Linalool, Cyclohexanone